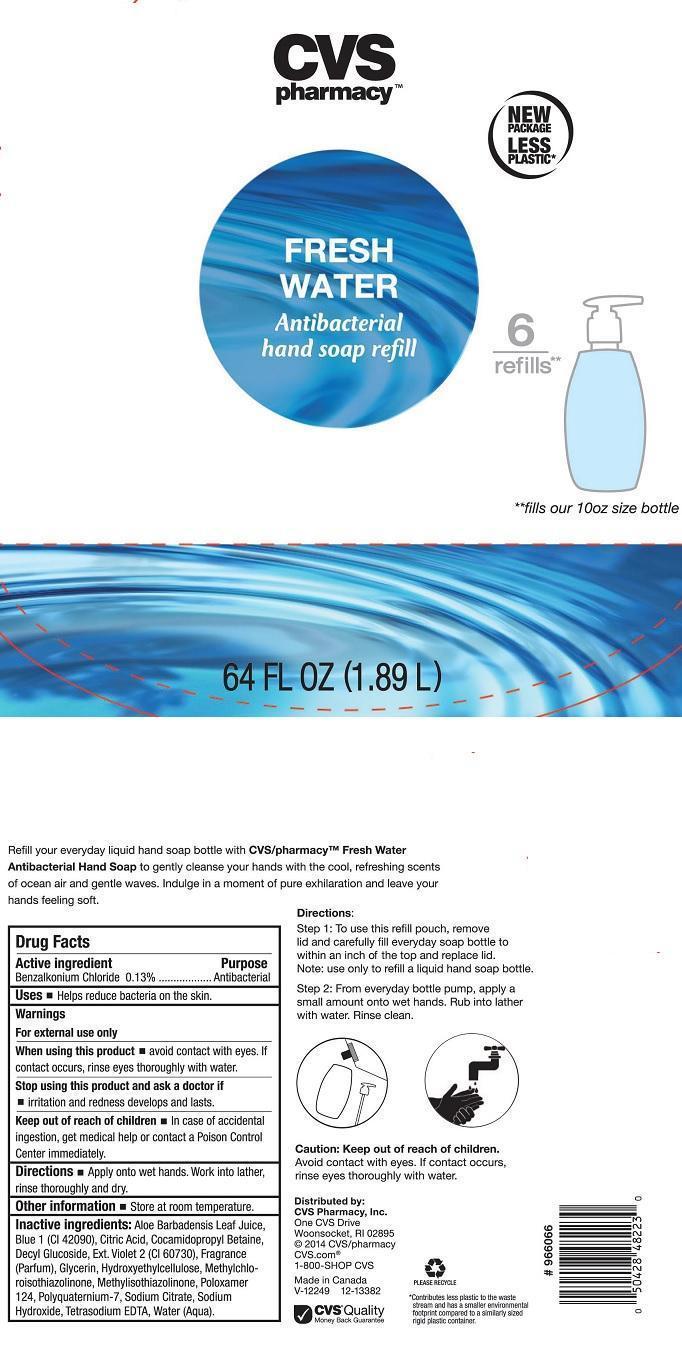 DRUG LABEL: CVS PHARMACY
NDC: 59779-723 | Form: LIQUID
Manufacturer: CVS PHARMACY
Category: otc | Type: HUMAN OTC DRUG LABEL
Date: 20140508

ACTIVE INGREDIENTS: BENZALKONIUM CHLORIDE 1.3 mg/1 mL
INACTIVE INGREDIENTS: ALOE VERA LEAF; FD&C BLUE NO. 1; CITRIC ACID MONOHYDRATE; COCAMIDOPROPYL BETAINE; DECYL GLUCOSIDE; EXT. D&C VIOLET NO. 2; GLYCERIN; HYPROMELLOSES; METHYLCHLOROISOTHIAZOLINONE; METHYLISOTHIAZOLINONE; POLOXAMER 124; POLYQUATERNIUM-7 (70/30 ACRYLAMIDE/DADMAC; 1600000 MW); SODIUM CITRATE; SODIUM HYDROXIDE; EDETATE SODIUM; WATER

DRUG FACTS

ACTIVE INGREDIENT

BENZALKONIUM CHLORIDE 0.13%

PURPOSE

ANTIBACTERIAL

USES

HELPS REDUCE BACTERIA ON THE SKIN

WARNINGS

FOR EXTERNAL USE ONLY

WHEN USING THIS PRODUCT

AVOID CONTACT WITH EYES. IF CONTACT OCCURS, RINSE EYES THOROUGHLY WITH WATER

STOP USING THIS PRODUCT AND ASK A DOCTOR IF

IRRITATION AND REDNESS DEVELOPS AND LASTS

KEEP OUT OF REACH OF CHILDREN

IN CASE OF ACCIDENTAL INGESTION, GET MEDICAL HELP OR CONTACT A POISON CONTROL CENTER IMMEDIATELY

DIRECTIONS

APPLY ONTO WET HANDS. WORK INTO LATHER, RINSE THOROUGHLY AND DRY

OTHER INFORMATION

STORE AT ROOM TEMPERATURE

INACTIVE INGREDIENTS

ALOE BARBADENSIS LEAF JUICE, BLUE 1 (CI 42090), CITRIC ACID, COCAMIDOPROPYL BETAINE, DECYL GLUCOSIDE, EXT. VIOLET 2 (CI 60730), FRAGRANCE (PARFUM), GLYCERIN, HYDROXYETHYLCELLULOSE, METHYLCHLOROISOTHIAZOLINONE, METHYLISOTHIAZOLINONE, POLOXAMER 124, POLYQUATERNIUM-7, SODIUM CITRATE, SODIUM HYDROXIDE, TETRASODIUM EDTA, WATER (AQUA)